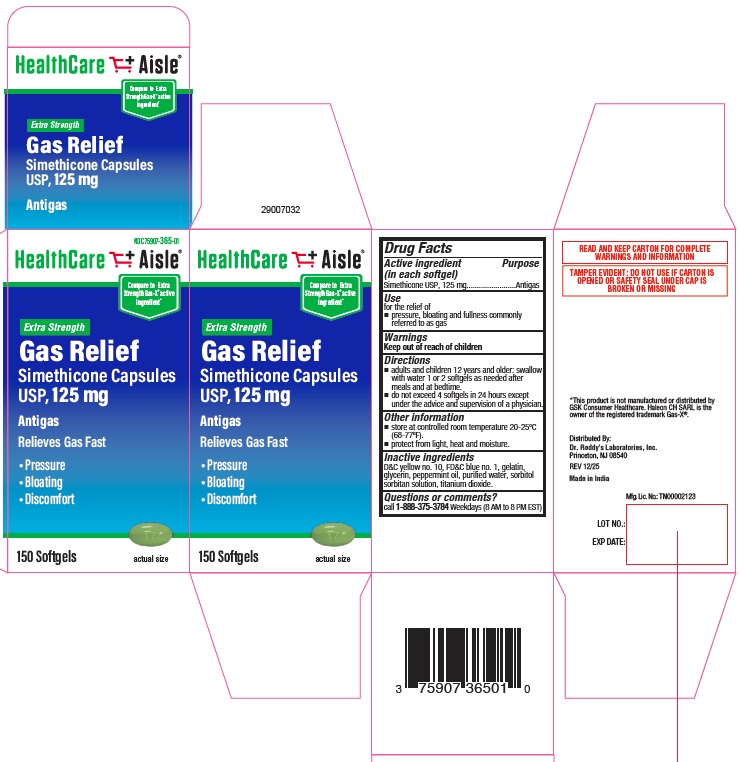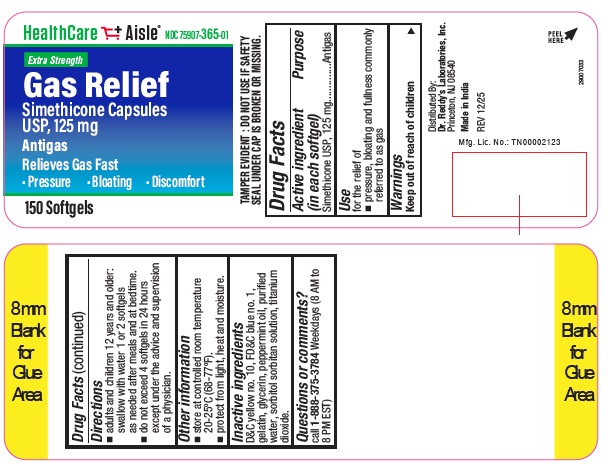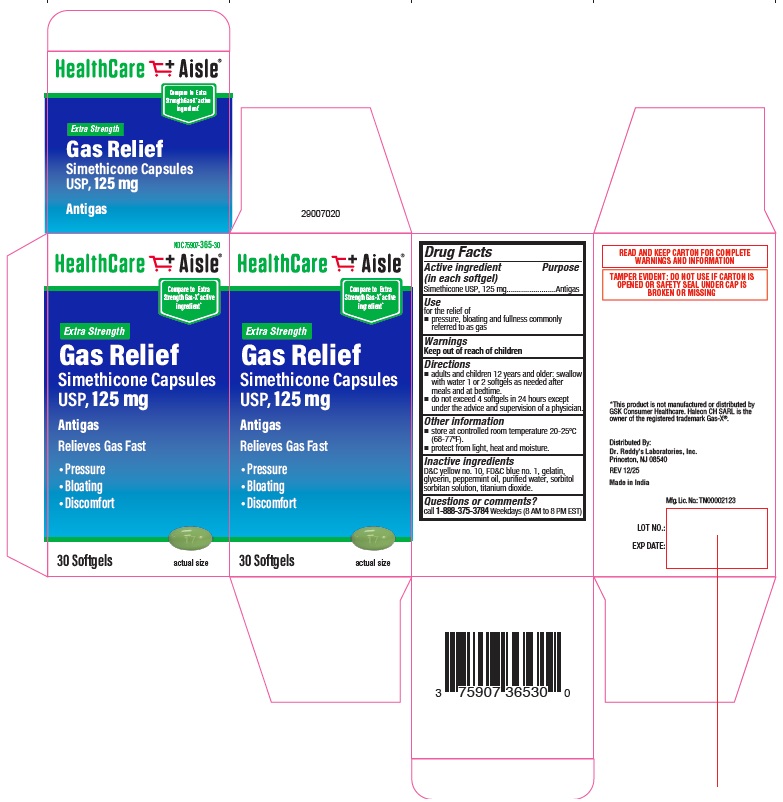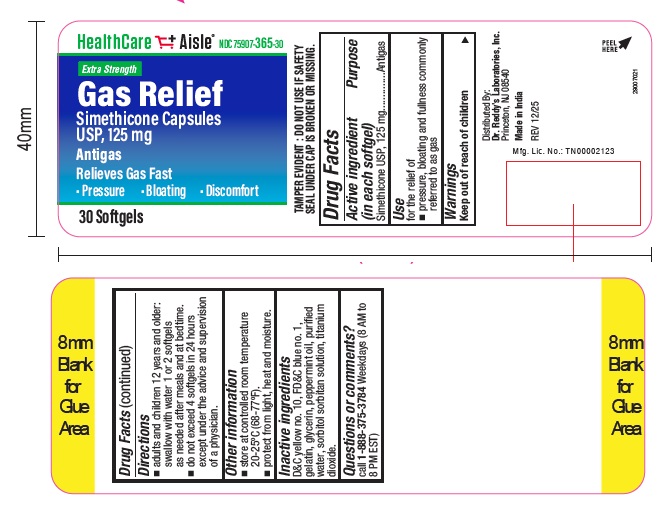 DRUG LABEL: Gas Relief
NDC: 75907-365 | Form: CAPSULE, LIQUID FILLED
Manufacturer: Dr. Reddy's Laboratories Inc.
Category: otc | Type: HUMAN OTC DRUG LABEL
Date: 20251215

ACTIVE INGREDIENTS: DIMETHICONE 125 mg/1 1
INACTIVE INGREDIENTS: D&C YELLOW NO. 10; TITANIUM DIOXIDE; GELATIN; PEPPERMINT OIL; SORBITOL; FD&C BLUE NO. 1; GLYCERIN; WATER

Simethicone Capsules USP, 125 mg

Active ingredient (in each Softgel)

Simethicone USP, 125 mg

Purpose

Antigas

Use

for the relief of

- pressure, bloating, and fullness commonly referred to as gas

Warnings

Keep out of reach of children

Directions

- adults and children 12 years and older: swallow with water 1 or 2 softgels as needed after meals and at bedtime
- do not exceed 4 softgels in 24 hours except under the advice and supervision of a physician

Other information

- store at controlled room temperature 20-25ºC (68-77ºF)
- protect from light, heat and moisture

Inactive ingredients

D&C yellow no.10, FD&C blue no. 1, gelatin, glycerin, peppermint oil, purified water, sorbitol sorbitan solution, titanium dioxide

Questions or comments?

call 1-888-375-3784 Weekdays (8 AM to 8 PM EST)

Principal Display Panel

NDC 75907-365-30

Compare to Extra Strength Gas-X ® active ingredient*

Gas Relief

Simethicone Capsules USP, 125 mg

Antigas

Relieves Gas Fast

Pressure, Bloating, Discomfort

30 Softgels

*This product is not manufactured or distributed by GSK Consumer Healthcare. Haleon CH SARL is the owner of the registered trademark Gas-X®.

Distributed By:

Dr. Reddy's Laboratories, Inc.

Princeton, NJ 08540

REV 12/25

Made in India

Principal Display Panel

NDC 75907-365-01

Compare to Extra Strength Gas-X ® active ingredient*

Gas Relief

Simethicone Capsules USP, 125 mg

Antigas

Relieves Gas Fast

Pressure, Bloating, Discomfort

150 Softgels

*This product is not manufactured or distributed by GSK Consumer Healthcare. Haleon CH SARL is the owner of the registered trademark Gas-X®.

Distributed By:

Dr. Reddy's Laboratories, Inc.

Princeton, NJ 08540

REV 12/25

Made in India